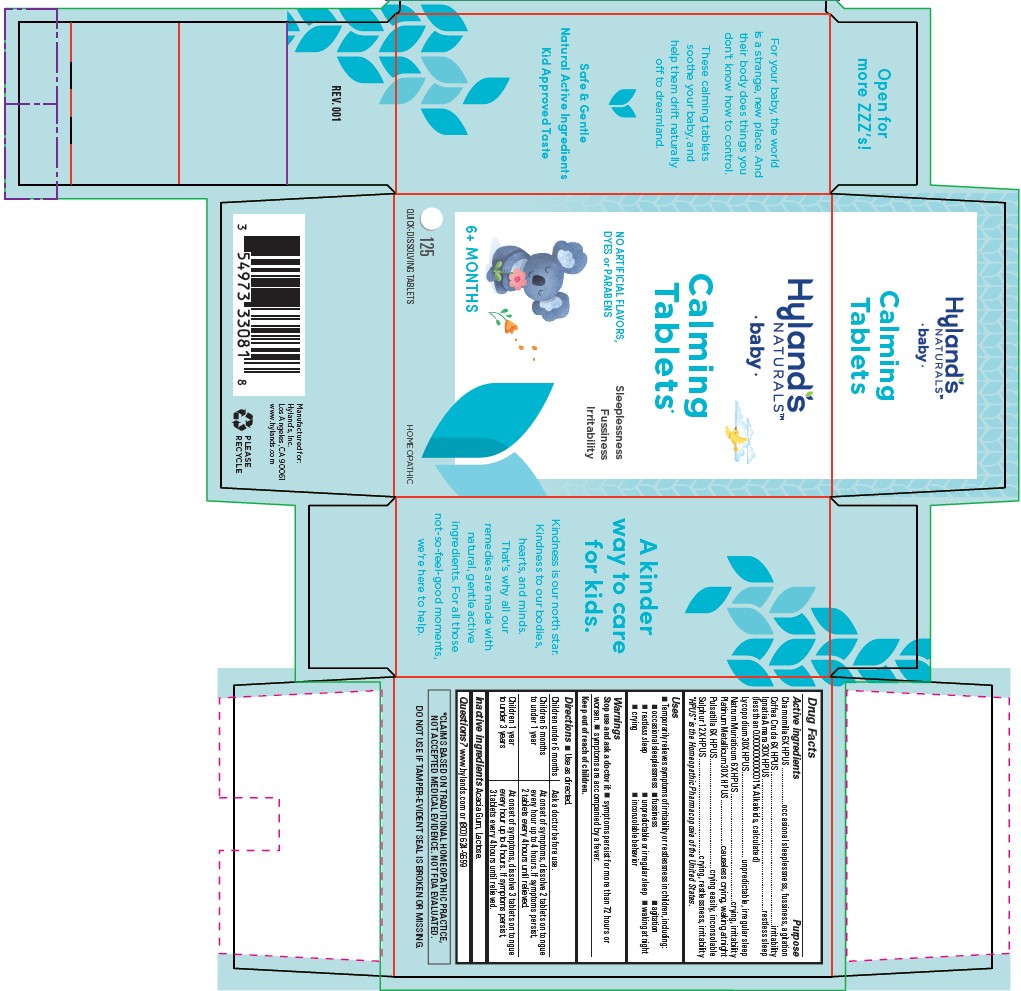 DRUG LABEL: BABY CALMING
NDC: 54973-3308 | Form: TABLET
Manufacturer: Hyland's
Category: homeopathic | Type: HUMAN OTC DRUG LABEL
Date: 20211220

ACTIVE INGREDIENTS: MATRICARIA RECUTITA 6 [hp_X]/1 1; ARABICA COFFEE BEAN 6 [hp_X]/1 1; STRYCHNOS IGNATII SEED 30 [hp_X]/1 1; LYCOPODIUM CLAVATUM SPORE 30 [hp_X]/1 1; SODIUM CHLORIDE 6 [hp_X]/1 1; PLATINUM 30 [hp_X]/1 1; ANEMONE PULSATILLA 6 [hp_X]/1 1; SULFUR 12 [hp_X]/1 1
INACTIVE INGREDIENTS: ACACIA; LACTOSE, UNSPECIFIED FORM

Hyland's Naturals Baby Calming

Drug Facts

ACTIVE INGREDIENT

Active ingredients | Purpose
Chamomilla 6X HPUS | occasional sleeplessness, fussiness, and agitation
Coffea Cruda 6X HPUS | irritability
Ignatia Amara 30X HPUS (less than 0.0000000000001% Alkaloids, calculated) | restless sleep
Lycopodium 30X HPUS | unpredictable, irregular sleep
Natrum Muriaticum 6X HPUS | crying, irritability
Platinum Metallicum 30X HPUS | causeless crying, waking at night
Pulsatilla 6X HPUS | cries easily, inconsolable
Sulphur 12X HPUS | crying, restlessness, irritability
"HPUS" indicates that the active ingredients are in the official Homeopathic Pharmacopœia of the United States.

Uses

■ Temporarily relieves symptoms of irritability or restlessness in children, including:

■ occasional sleeplessness ■ fussiness ■ agitation
■ restless sleep ■ unpredictable or irregular sleep ■ waking at night
■ crying ■ inconsolable behavior

Warnings

Stop use and ask a doctor if: ■ symptoms persist for more than 72 hours or worsen.

■ symptoms are accompanied by a fever.

Keep out of reach of children.

Directions

■ Use as directed.

Children under 6 months | Ask a doctor before use.
Children 6 months to under 1 year | At onset of symptoms, dissolve 2 tablets on tongue every hour up to 4 hours. If symptoms persist, 2 tablets every 4 hours until relieved.
Children 1 year to under 3 years | At onset of symptoms, dissolve 3 tablets on tongue every hour up to 4 hours. If symptoms persist, 3 tablets every 4 hours until relieved.

Inactive ingredients

Acacia Gum, Lactose.

Questions or comments?

www.hylands.com or (800) 624-9659

*CLAIMS BASED ON TRADITIONAL HOMEOPATHIC PRACTICE,
NOT ACCEPTED MEDICAL EVIDENCE. NOT FDA EVALUATED.

DO NOT USE IF TAMPER-EVIDENT SEAL IS BROKEN OR MISSING.

Indications and Usage

■ Temporarily relieves symptoms of irritability or restlessness in children, including:

■ occasional sleeplessness ■ fussiness ■ agitation
■ restless sleep ■ unpredictable or irregular sleep ■ waking at night
■ crying ■ inconsolable behavior

Dosage and Administration (Directions)

■ Use as directed.

Children under 6 months | Ask a doctor before use.
Children 6 months to under 1 year | At onset of symptoms, dissolve 2 tablets on tongue every hour up to 4 hours. If symptoms persist, 2 tablets every 4 hours until relieved.
Children 1 year to under 3 years | At onset of symptoms, dissolve 3 tablets on tongue every hour up to 4 hours. If symptoms persist, 3 tablets every 4 hours until relieved.

PACKAGE LABEL - PRINCIPAL DISPLAY PANEL

Hyland's

Naturals™

•baby•

Calming

Tablets*

NO ARTIFICIAL FLAVORS,

DYES or PARABENS

Sleeplessness

Fussiness

Irritability

6+ MONTHS

125

QUICK-DISSOLVING TABLETS

HOMEOPATHIC